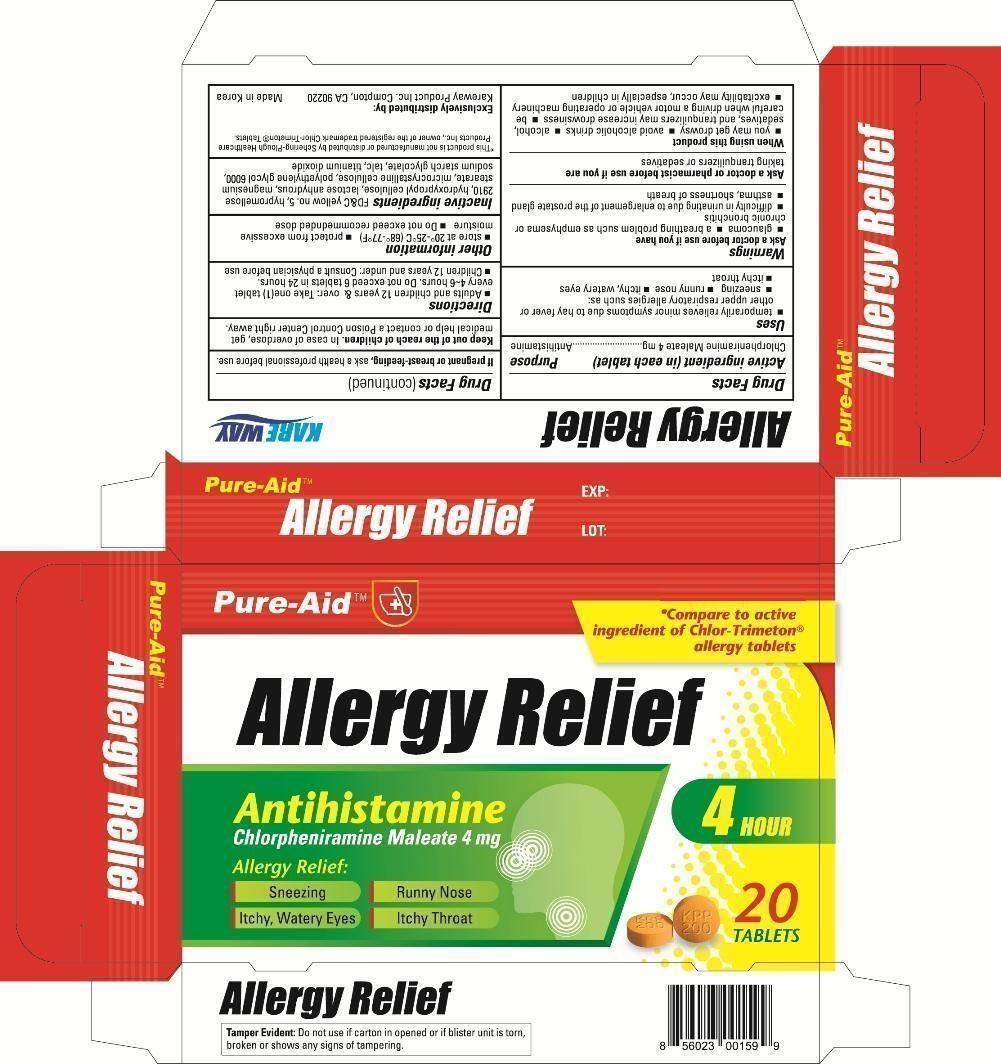 DRUG LABEL: Allergy Relief
NDC: 67510-0159 | Form: TABLET
Manufacturer: Kareway Product, Inc.
Category: otc | Type: HUMAN OTC DRUG LABEL
Date: 20130215

ACTIVE INGREDIENTS: CHLORPHENIRAMINE MALEATE 4 mg/1 1
INACTIVE INGREDIENTS: MICROCRYSTALLINE WAX; ANHYDROUS LACTOSE; SODIUM STARCH GLYCOLATE TYPE A POTATO; STARCH, CORN; CROSPOVIDONE; SILICON DIOXIDE; STEARIC ACID; HYPROMELLOSES; FD&C RED NO. 40; FD&C YELLOW NO. 5; TITANIUM DIOXIDE; POLYETHYLENE GLYCOLS; ETHANETHIOL

Drug Facts

Active ingredient (in each tablet)

Chlorpheniramine Maleate 4mg

Purpose

Antihistamine

Uses

- temporarily relieves minor symptoms due to hay fever or other upper respiratory allergies such as:
-
  - sneezing
  - runny nose
  - itchy, watery eyes
  - itchy throat

Warnings

Ask a doctor before use it you have

- glaucoma
- a breathing problem such as emphysema or chronic bronchitis
- difficulty in urinating due to enlargement of the prostate gland
- asthma, shortness of breath

Ask a doctor or pharmacist before use if you are

taking sedatives or tranquilizers

When using this product

- you may get drowsy
- avoid alcoholic drinks
- alcohol, sedatives, and tranquilizers may increase drowsiness
- be careful when driving a motor vehicle or operating machinery
- excitability may occur, especially in children

If pregnant or breast-feeding,

ask a health professional before use.

Keep out of reach of children.

In case of accidental overdose get medical help or contact a Poison Control Center right away.

Directions

- Adults and children 12 years and over: Take one (1) tablet every 4 to 6 hours. Do not exceed 6 tablets in 24 hours.
- Children 12 years and under: Consult a physician before use

Other information

- store at 20° to 25°C (68°-67°F)
- protect from excessive moisture

- Do not exceed recommended dose

Inactive ingredients

microcrystalline cellulose, lactose anhydrous, sodium starch glycolate, corn starch glycolate, crospovidone, silicon dioxide, stearic acid, hypromellose, FDC red no.40, FDC yellow no.5, titanium dioxide, polyethyleneglycol, ethanol